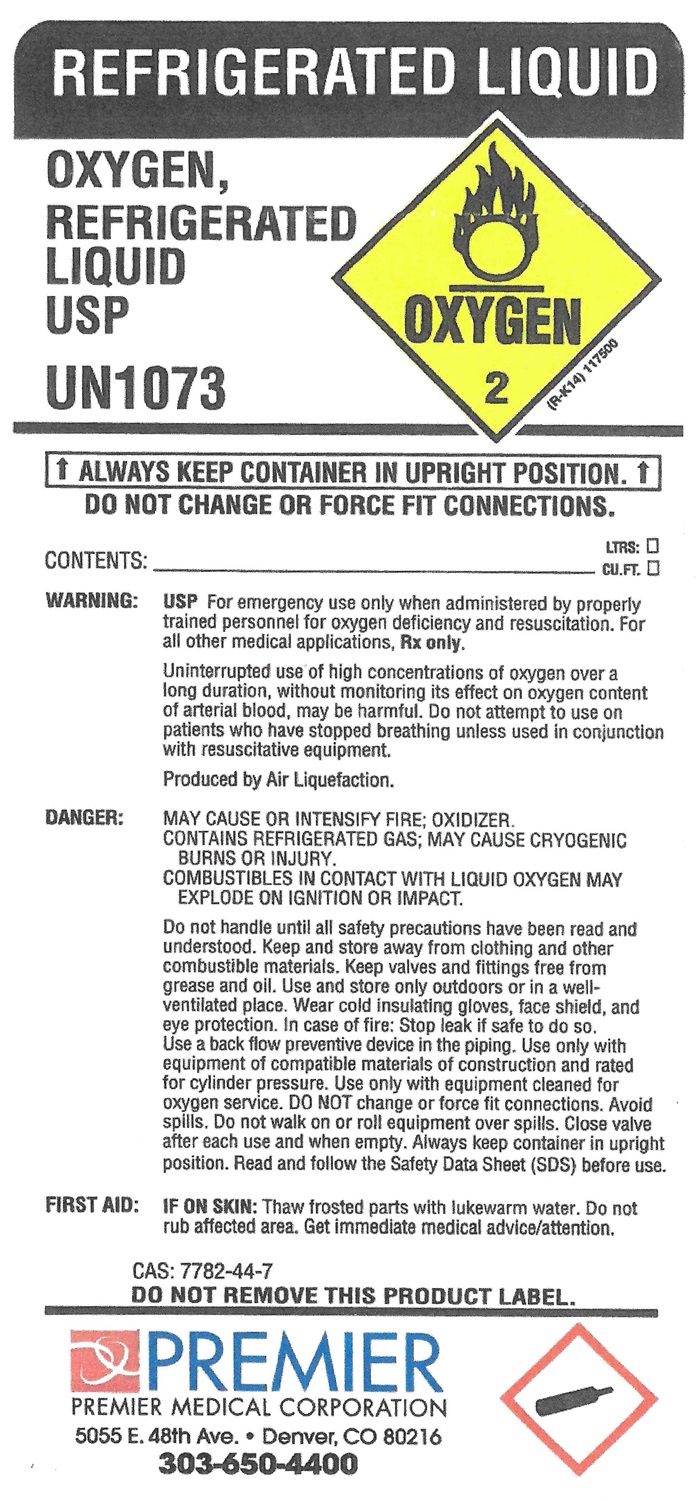 DRUG LABEL: OXYGEN
NDC: 61604-9068 | Form: GAS
Manufacturer: Premier Medical Corporation
Category: prescription | Type: HUMAN PRESCRIPTION DRUG LABEL
Date: 20180303

ACTIVE INGREDIENTS: OXYGEN 99 L/100 L

OXYGEN REFRIGERATED LIQUID USP UN1073 CONTENTS_________ LITERS ALWAYS KEEP CONTAINER IN UPRIGHT POSITION. WARNING: DO NOT CHANGE OR FORCE FIT CONNECTIONS. EXTREMELY COLD LIQUID AND GAS UNDER PRESSURE. VIGOROUSLY ACCELERATES COMBUSTION. NO SMOKING IN THE PRESENCE OF OXYGEN OR A FIRE MAY RESULT. COMBUSTIBLES IN CONTACT WITH LIQUID OXYGEN MAY EXPLODE ON IGNITION OR IMPACT. CAN CAUSE SEVERE FROSTBITE. KEEP OIL, GREASE AND COMBUSTIBLES AWAY. USE ONLY WITH EQUIPMENT CLEANED FOR OXYGEN SERVICE. STORE AND USE WITH ADEQUATE VENTILATION. DO NOT GET LIQUID IN EYES, ON SKIN OR CLOTHING. FOR LIQUID WITHDRAWAL, WEAR FACE SHIELD AND GLOVES. DO NOT DROP. USE SUITABLE HAND TRUCK FOR CONTAINER MOVEMENT. AVOID SPILLS. DO NOT WALK OR ROLL EQUIPMENT OVER SPILLS CONTAINER TEMPERATURE SHOULD NOT EXCEED 52C (125 F) CLOSE VALVE AFTER EACH USE AND WHEN EMPTY. USE A BACK FLOW PREVENTATIVE DEVICE IN THE PIPING. USE IN ACCORDANCE WITH THE MATERIAL SAFETY DATA SHEET (MSDS)
FIRST AID: IN CASE OF FROSTBITE OBTAIN MEDICAL TREATMENT IMMEDIATELY.
WARNING: FOR EMERGENCY USE ONLY WHEN ADMINISTERED BY PROPERLY TRAINED PERSONNEL FOR OXYGEN DEFICIENCY AND RESUSCITATION. FOR ALL OTHER MEDICAL APPLICATIONS Rx ONLY. UNINTERRUPTED USE OF HIGH CONCENTRATIONS OF OXYGEN OVER A LONG DURATION WITHOUT MONITORING ITS EFFECT ON OXYGEN CONTENT OF ARTERIAL BLOOD MAY BE HARMFUL. USE ONLY WITH PRESSURE REDUCING EQUIPMENT AND APPARATUS DESIGNED FOR OXYGEN. DO NOT ATTEMPT TO USE ON PATIENTS WHO HAVE STOPPED BREATHING, UNLESS USED IN CONJUNCTION WITH RESUSCITATIVE EQUIPMENT. PRODUCED BY AIR LIQUEFACTION. DO NOT REMOVE THIS PRODUCT LABEL.